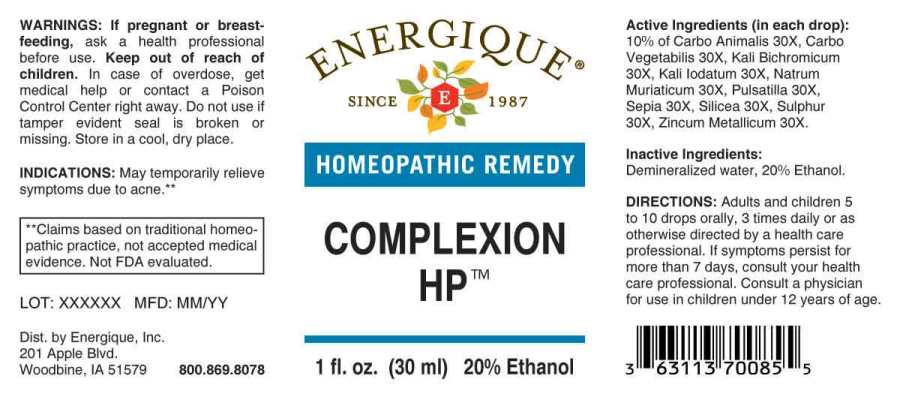 DRUG LABEL: Complexion
NDC: 44911-0565 | Form: LIQUID
Manufacturer: Energique, Inc.
Category: homeopathic | Type: HUMAN OTC DRUG LABEL
Date: 20241024

ACTIVE INGREDIENTS: CARBO ANIMALIS 30 [hp_X]/1 mL; ACTIVATED CHARCOAL 30 [hp_X]/1 mL; POTASSIUM DICHROMATE 30 [hp_X]/1 mL; POTASSIUM IODIDE 30 [hp_X]/1 mL; SODIUM CHLORIDE 30 [hp_X]/1 mL; PULSATILLA PRATENSIS WHOLE 30 [hp_X]/1 mL; SEPIA OFFICINALIS JUICE 30 [hp_X]/1 mL; SILICON DIOXIDE 30 [hp_X]/1 mL; SULFUR 30 [hp_X]/1 mL; ZINC 30 [hp_X]/1 mL
INACTIVE INGREDIENTS: WATER; ALCOHOL

DRUG FACTS:

ACTIVE INGREDIENTS:

(in each drop): 10% of Carbo Animalis 30X, Carbo Vegetabilis 30X, Kali Bichromicum 30X, Kali Iodatum 30X, Natrum Muriaticum 30X, Pulsatilla (Pratensis) 30X, Sepia 30X, Silicea 30X, Sulphur 30X, Zincum Metallicum 30X.

INDICATIONS:

May temporarily relieve symptoms due to acne.**

**Claims based on traditional homeopathic practice, not accepted medical evidence. Not FDA evaluated.

WARNINGS:

If pregnant or breastfeeding, ask a health professional before use.

Keep out of reach of children. In case of overdose, get medical help or contact a Poison Control Center right away.

Do not use if tamper evident seal is broken or missing.

Store in a cool, dry place.

Keep out of reach of children. In case of overdose, get medical help or contact a Poison Control Center right away.

DIRECTIONS:

Adults and children 5 to 10 drops orally, 3 times daily or as otherwise directed by a health care professional. If symptoms persist for more than 7 days, consult your health care professional. Consult a physician for use in children under 12 years of age.

INDICATIONS:

May temporarily relieve symptoms due to acne.**

**Claims based on traditional homeopathic practice, not accepted medical evidence. Not FDA evaluated.

INACTIVE INGREDIENTS:

Demineralized water, 20% Ethanol.

QUESTIONS:

Dist. by Energique, Inc.
201 Apple Blvd.
Woodbine, IA 51579 800.869.8078

PACKAGE LABEL DISPLAY:

ENERGIQUE
SINCE 1987
HOMEOPATHIC REMEDY
COMPLEXION HP
1 fl. oz. (30 ml)